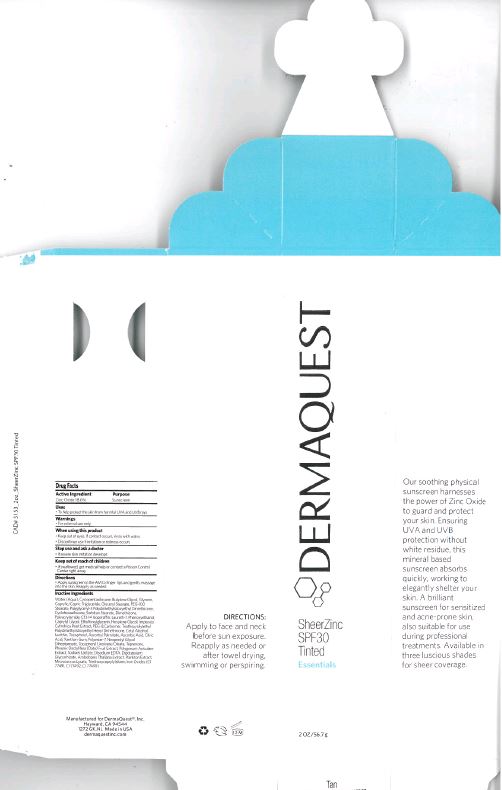 DRUG LABEL: SheerZinc SPF 30 Tinted - Tan
NDC: 62742-4095 | Form: CREAM
Manufacturer: Allure Labs Inc
Category: otc | Type: HUMAN OTC DRUG LABEL
Date: 20171128

ACTIVE INGREDIENTS: ZINC OXIDE 186 mg/1 g
INACTIVE INGREDIENTS: WATER; DIMETHICONE CROSSPOLYMER (450000 MPA.S AT 12% IN CYCLOPENTASILOXANE); BUTYLENE GLYCOL; GLYCERIN; MEDIUM-CHAIN TRIGLYCERIDES; GLYCERYL STEARATE SE; PEG-100 STEARATE; POLYGLYCERYL-3 POLYDIMETHYLSILOXYETHYL DIMETHICONE (4000 MPA.S); CYCLOMETHICONE 6; SORBITAN MONOSTEARATE; DIMETHICONE; C13-14 ISOPARAFFIN; LAURETH-7; PHENOXYETHANOL; CAPRYLYL GLYCOL; ETHYLHEXYLGLYCERIN; HEXYLENE GLYCOL; IMPERATA CYLINDRICA ROOT; POLYETHYLENE GLYCOL 400; CARBOMER 1342; CETYL ALCOHOL; LECITHIN, SOYBEAN; TOCOPHEROL; ASCORBYL PALMITATE; ASCORBIC ACID; CITRIC ACID MONOHYDRATE; XANTHAN GUM; POLYESTER-7; NEOPENTYL GLYCOL DIHEPTANOATE; .ALPHA.-TOCOPHEROL LINOLEATE, D-; TEPRENONE; DATE; POLYGONUM AVICULARE TOP; SODIUM LACTATE; EDETATE DISODIUM ANHYDROUS; GLYCYRRHIZINATE DIPOTASSIUM; ARABIDOPSIS THALIANA; MICROCOCCUS LUTEUS; TRIETHOXYCAPRYLYLSILANE; FERRIC OXIDE RED; FERRIC OXIDE YELLOW; FERROSOFERRIC OXIDE

Drug Facts

Active Ingredient: Zinc oxide - 18.6%

Purpose: Sunscreen

Uses:

- To help protect the skin from harmful UVA and UVB rays

Warnings: For external use only

When using this product:

- Keep out of eyes. If contact occurs, rinse with water.
- Discontinue use if irritation or redness occurs.

Stop use and ask a doctor

- If severe skin irritation developes

Keep out of reach of children:

- If swallowed, get medical help or contact a Poison Cpntrol center right away.

Directions:

- Apply sunscreen in the AM to finger tips and gently massage into the skin. Reapply as needed.

INACTIVE INGREDIENT

Other Ingredients: Water (Aqua), Cyclopentasiloxane, Butylene glycol, glycerin, Caprylic/Capric triglyceride, Glycerin Stearate, PEG-100 Stearate, Polyglyceryl-3 Polymethylsiloxyeethyl Dimethicon, Cyclohexasiloxane, Sorbitan Stearate, Dimethicone, Polyacrylamide, C13-14 Isoparaffin, Laureth-7,phenoxyethanol, Caprylyl Glycol, Ethylhexyglycerin, Hexylene glycol, Imperata Cylindrica Root Extract, PEG-8, Carbomer, triethoxysilylethyl Polydimethylsiloxyethyl Hexyl Dimethicone, Cetyl Alcohol, Lecithin, Tocopherol, Ascorbyl Palmitate, Ascorbic Acid, Citric Acid, Xanthan gum, Polyester-7, Neopentyl Glycol Diheptanoate, tocopherol Linoleate/Oleate, Teprenone, Phoenix Dactylifera (Date) Fruit Extract, Polygonum Aviculare Extract, Sodium Lactate, Disodium EDTA, Dipotassium Glycyrrhizate, Arabidopsis Thaliana Extract, Plankton Extract, Micrococcus Lysate, Triethoxycaprylysilane, Iron Oxides (CI77491, CI77492, CI77499)

PACKAGE LABEL

Manufactured for DermaQuest, Inc.

Hayward, CA 94544

1272 GK, NL Made in USA

dermaquestinc.com